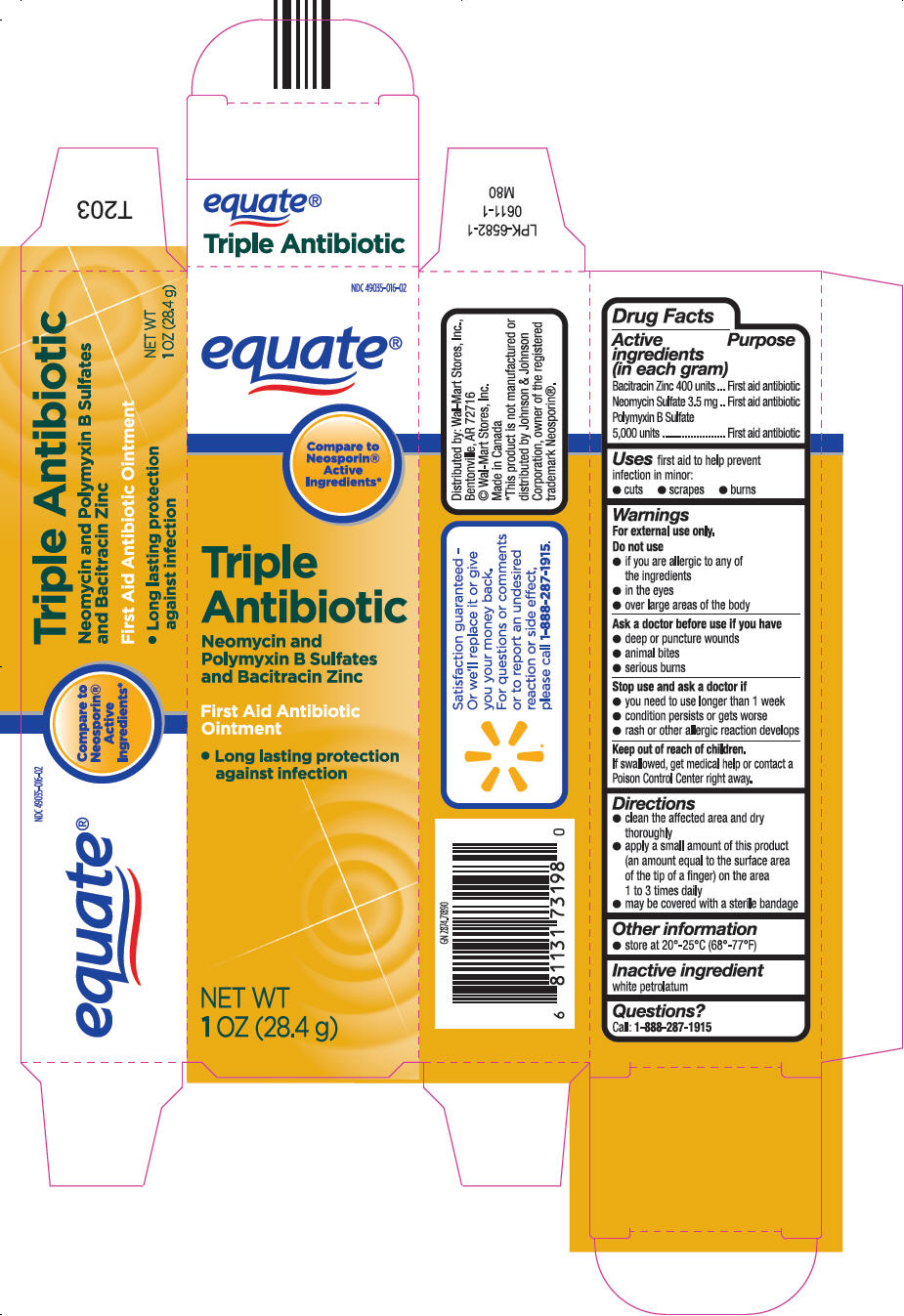 DRUG LABEL: Triple Antibiotic
NDC: 49035-016 | Form: OINTMENT
Manufacturer: Wal-Mart Stores, Inc.
Category: otc | Type: HUMAN OTC DRUG LABEL
Date: 20250714

ACTIVE INGREDIENTS: BACITRACIN ZINC 400 [iU]/1 g; NEOMYCIN SULFATE 3.5 mg/1 g; POLYMYXIN B SULFATE 5000 [iU]/1 g
INACTIVE INGREDIENTS: PETROLATUM

Triple Antibiotic Ointment

Drug Facts

ACTIVE INGREDIENT

Active ingredients (in each gram) | Purpose
Bacitracin Zinc 400 units | First aid antibiotic
Neomycin Sulfate 3.5 mg | First aid antibiotic
Polymyxin B Sulfate 5,000 units | First aid antibiotic

Uses

first aid to help prevent infection in minor:

- cuts
- scrapes
- burns

Warnings

For external use only.

Do not use

- if you are allergic to any of the ingredients
- in the eyes
- over large areas of the body

Ask a doctor before use if you have

- deep or puncture wounds
- animal bites
- serious burns

Stop use and ask a doctor if

- you need to use longer than 1 week
- condition persists or gets worse
- rash or other allergic reaction develops

Keep out of reach of children.

If swallowed, get medical help or contact a Poison Control Center right away.

Directions

- clean the affected area and dry thoroughly
- apply a small amount of this product (an amount equal to the surface area of the tip of a finger) on the area 1 to 3 times daily
- may be covered with a sterile bandage

Other information

- store at 20°-25°C (68°-77°F)

Inactive ingredient

white petrolatum

Questions?

call: 1-888-287-1915

Distributed by: Wal-Mart Stores, Inc.,
Bentonville, AR 72716

PRINCIPAL DISPLAY PANEL - 28.4 g Tube Carton

NDC 49035-016-02

equate®

Compare to
Neosporin ®
Active
Ingredients*

Triple
Antibiotic

Neomycin and
Polymyxin B Sulfates
and Bacitracin Zinc

First Aid Antibiotic
Ointment

- Long lasting protection
  against infection

NET WT
1OZ (28.4 g)